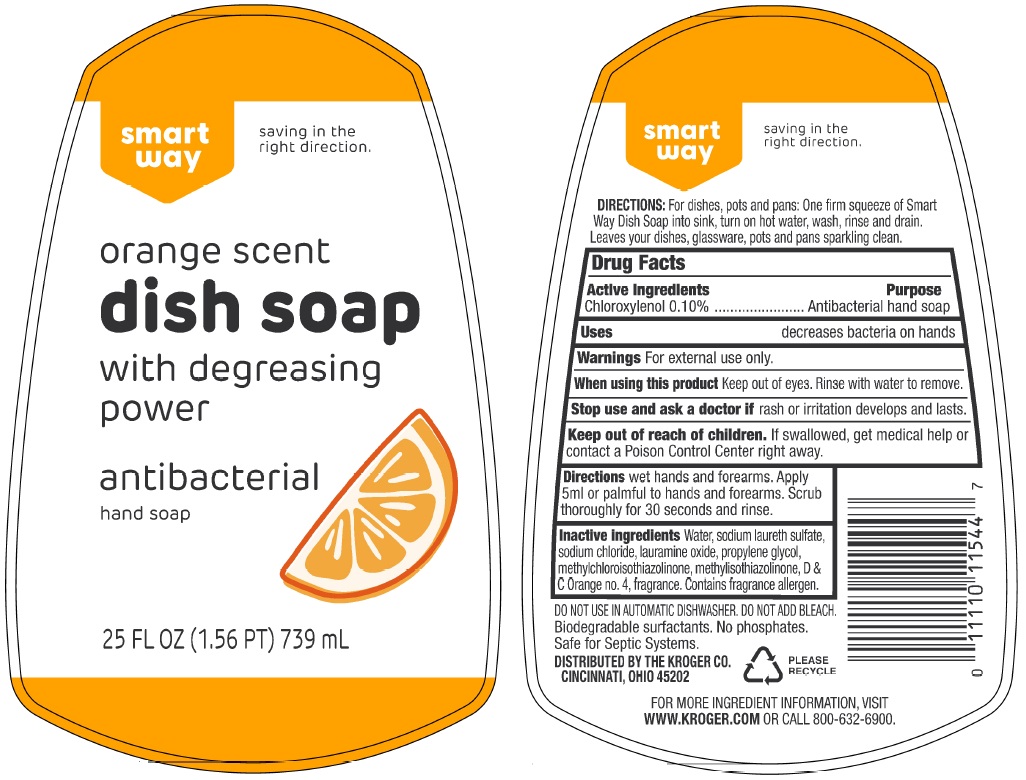 DRUG LABEL: smart way orange scent dish
NDC: 73487-007 | Form: SOAP
Manufacturer: Korex Chicago LLC
Category: otc | Type: HUMAN OTC DRUG LABEL
Date: 20241129

ACTIVE INGREDIENTS: CHLOROXYLENOL 0.10 g/100 mL
INACTIVE INGREDIENTS: WATER; SODIUM LAURETH-3 SULFATE; SODIUM CHLORIDE; LAURAMINE OXIDE; PROPYLENE GLYCOL; METHYLCHLOROISOTHIAZOLINONE; METHYLISOTHIAZOLINONE; D&C ORANGE NO. 4

smart way orange scent dish soap

Active ingredients

Chloroxylenol 0.10%

Purpose

Antibacterial hand soap

Uses

decreases bacteria on hands

Warnings

For external use only.

When using this product Keep out of eyes. Rinse with water to remove.

Stop use and ask a doctor if rash or irritation develops and lasts.

Keep out of reach of children. If swallowed, get medical help or contact a Poison Control Center right away.

Directions

wet hands and forearms. Apply 5ml or palmful to hands and forearms. Scrub thoroughly for 30 seconds and rinse.

Inactive ingredients

Water, sodium laureth sulfate, sodium chloride, lauramine oxide, propylene glycol, methylchloroisothiazolinone, methylisothiazolinone, D & C Orange no.4, fragrance. Contains fragrance allergen.

saving in the right direction.

with degreasing power

antibacterial hand soap

DIRECTIONS: For dishes, pots and pans: One firm squeeze of Smart Way Dish Soap into sink, turn on hot water, wash, rinse and drain. Leaves your dishes, glassware, pots and pans sparkling clean.

DO NOT USE IN AUTOMATIC DISHWASHER. DO NOT ADD BLEACH.

Biodegradable surfactants. No phosphates.

Safe for Septic Systems.

DISTRIBUTED BY THE KROGER CO.

CINCINNATI, OHIO 45202

PLEASE RECYCLE

FOR MORE INGREDIENT INFORMATION, VISIT
WWW.KROGER.COM OR CALL 800-632-6900.